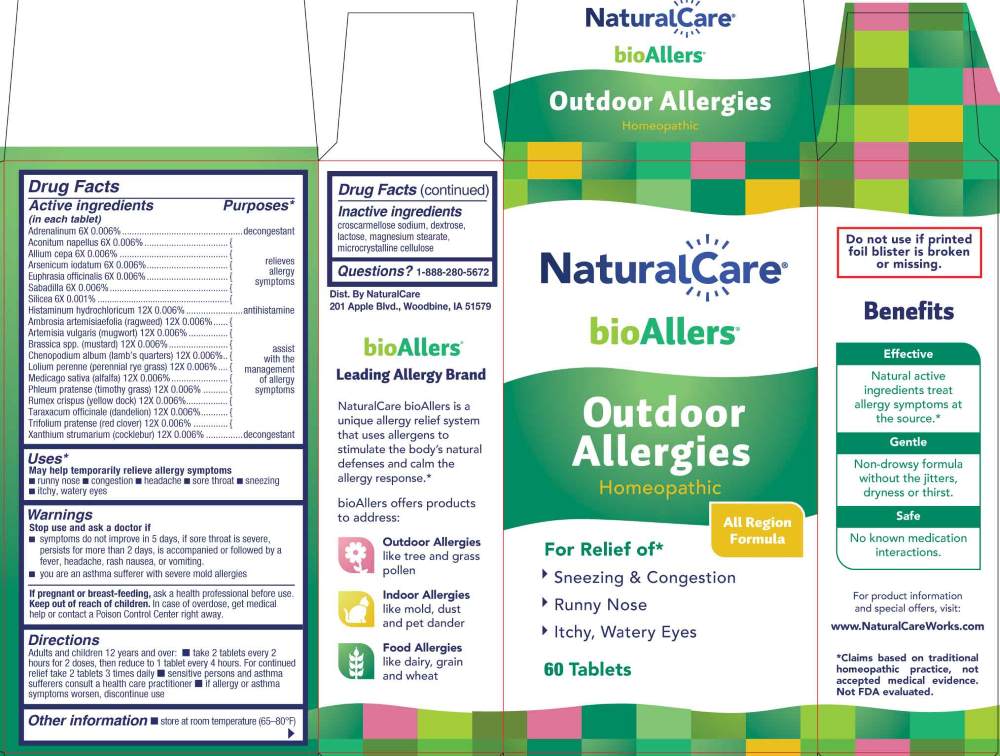 DRUG LABEL: Outdoor Allergies
NDC: 70163-0007 | Form: TABLET
Manufacturer: NaturalCare
Category: homeopathic | Type: HUMAN OTC DRUG LABEL
Date: 20260223

ACTIVE INGREDIENTS: ACONITUM NAPELLUS WHOLE 6 [hp_X]/1 1; EPINEPHRINE 6 [hp_X]/1 1; ONION 6 [hp_X]/1 1; AMBROSIA ARTEMISIIFOLIA WHOLE 12 [hp_X]/1 1; ARSENIC TRIIODIDE 6 [hp_X]/1 1; ARTEMISIA VULGARIS POLLEN 12 [hp_X]/1 1; BRASSICA RAPA SUBSP. OLEIFERA POLLEN 12 [hp_X]/1 1; CHENOPODIUM ALBUM POLLEN 12 [hp_X]/1 1; EUPHRASIA STRICTA 6 [hp_X]/1 1; HISTAMINE DIHYDROCHLORIDE 12 [hp_X]/1 1; LOLIUM PERENNE POLLEN 12 [hp_X]/1 1; MEDICAGO SATIVA POLLEN 12 [hp_X]/1 1; PHLEUM PRATENSE POLLEN 12 [hp_X]/1 1; RUMEX CRISPUS POLLEN 12 [hp_X]/1 1; SCHOENOCAULON OFFICINALE SEED 6 [hp_X]/1 1; SILICON DIOXIDE 6 [hp_X]/1 1; TARAXACUM OFFICINALE POLLEN 12 [hp_X]/1 1; TRIFOLIUM PRATENSE POLLEN 12 [hp_X]/1 1; XANTHIUM STRUMARIUM POLLEN 12 [hp_X]/1 1
INACTIVE INGREDIENTS: CROSCARMELLOSE SODIUM; DEXTROSE, UNSPECIFIED FORM; LACTOSE MONOHYDRATE; MAGNESIUM STEARATE; MICROCRYSTALLINE CELLULOSE

DRUG FACTS:

ACTIVE INGREDIENT:

(in each tablet) Adrenalinum 6X 0.006%, Aconitum Napellus 6X 0.006%, Allium Cepa 6X 0.006%, Arsenicum Iodatum 6X 0.006%, Euphrasia Officinalis 6X 0.006%, Sabadilla 6X 0.006%, Silicea 6X 0.001%, Histaminum Hydrochloricum 12X 0.006%, Ambrosia Artemisiaefolia (Ragweed) 12X 0.006%, Artemisia Vulgaris (Mugwort) 12X 0.006%, Brassica SSP. (Mustard) 12X 0.006%, Chenopodium Album (Lamb’s Quarters) 12X 0.006%, Lolium Perenne (Perennial Rye Grass) 12X 0.006%, Medicago Sativa (Alfalfa) 12X 0.006%, Phleum Pratense (Timothy Grass) 12X 0.006%, Rumex Crispus (Yellow Dock) 12X 0.006%, Taraxacum Officinale (Dandelion) 12X 0.006%, Trifolium Pratense (Red Clover) 12X 0.006%, Xanthium Strumarium (Cocklebur) 12X 0.006%.

PURPOSE:

Adrenalinum - decongestant, Aconitum Napellus – relieves allergy symptoms, Allium Cepa - relieves allergy symptoms, Arsenicum Iodatum - relieves allergy symptoms, Euphrasia Officinalis - relieves allergy symptoms, Sabadilla - relieves allergy symptoms, Silicea - relieves allergy symptoms, Histaminum Hydrochloricum - antihistamine, Ambrosia Artemisiaefolia (Ragweed) – assist with the management of allergy symptoms, Artemisia Vulgaris (Mugwort) - assist with the management of allergy symptoms, Brassica SSP. (Mustard) - assist with the management of allergy symptoms, Chenopodium Album (Lamb’s Quarters) - assist with the management of allergy symptoms, Lolium Perenne (Perennial Rye Grass) - assist with the management of allergy symptoms, Medicago Sativa (Alfalfa) - assist with the management of allergy symptoms, Phleum Pratense (Timothy Grass) - assist with the management of allergy symptoms, Rumex Crispus (Yellow Dock) - assist with the management of allergy symptoms, Taraxacum Officinale (Dandelion) - assist with the management of allergy symptoms, Trifolium Pratense (Red Clover) - assist with the management of allergy symptoms, Xanthium Strumarium (Cocklebur) - decongestant*

*Claims based on traditional homeopathic practice, not accepted medical evidence. Not FDA evaluated.

USES:

May help temporarily relieve allergy symptoms

■ runny nose ■ congestion ■ headache ■ sore throat ■ sneezing ■ itchy, watery eyes*

*Claims based on traditional homeopathic practice, not accepted medical evidence. Not FDA evaluated.

WARNINGS:

Stop use and ask a doctor if

■ symptoms do not improve in 5 days, if sore throat is severe, persists for more than 2 days, is accompanied or followed by a fever, headache, rash, nausea, or vomiting.

■ you are an asthma sufferer with severe mold allergies

If pregnant or breast-feeding, ask a health professional before use.

Keep out of reach of children. In case of overdose, get medical help or contact a Poison Control Center right away.

Do not use if printed foil blister is broken or missing.

■ Store at room temperature (65-80ºF)

KEEP OUT OF REACH OF CHILDREN:

In case of overdose, get medical help or contact a Poison Control Center right away.

DIRECTIONS:

Adults and children 12 years and over:

■ take 2 tablets every 2 hours for 2 doses, then reduce to 1 tablet every 4 hours. For continued relief take 2 tablets 3 times daily

■ sensitive persons and asthma sufferers consult a health care practitioner

■ if allergy or asthma symptoms worsen, discontinue use

INACTIVE INGREDIENTS:

croscarmellose sodium, dextrose, lactose, magnesium stearate, microcrystalline cellulose

QUESTIONS:

Dist. By NaturalCare

201 Apple Blvd.

Woodbine, IA 51579

www.NaturalCareWorks.com

1-888-280-5672

PACKAGE LABEL DISPLAY:

NaturalCare

bioAllers

Outdoor Allergies

Homeopathic

For Relief of*

Sneezing & Congestion

Runny Nose

Itchy, Watery Eyes

60 Tablets